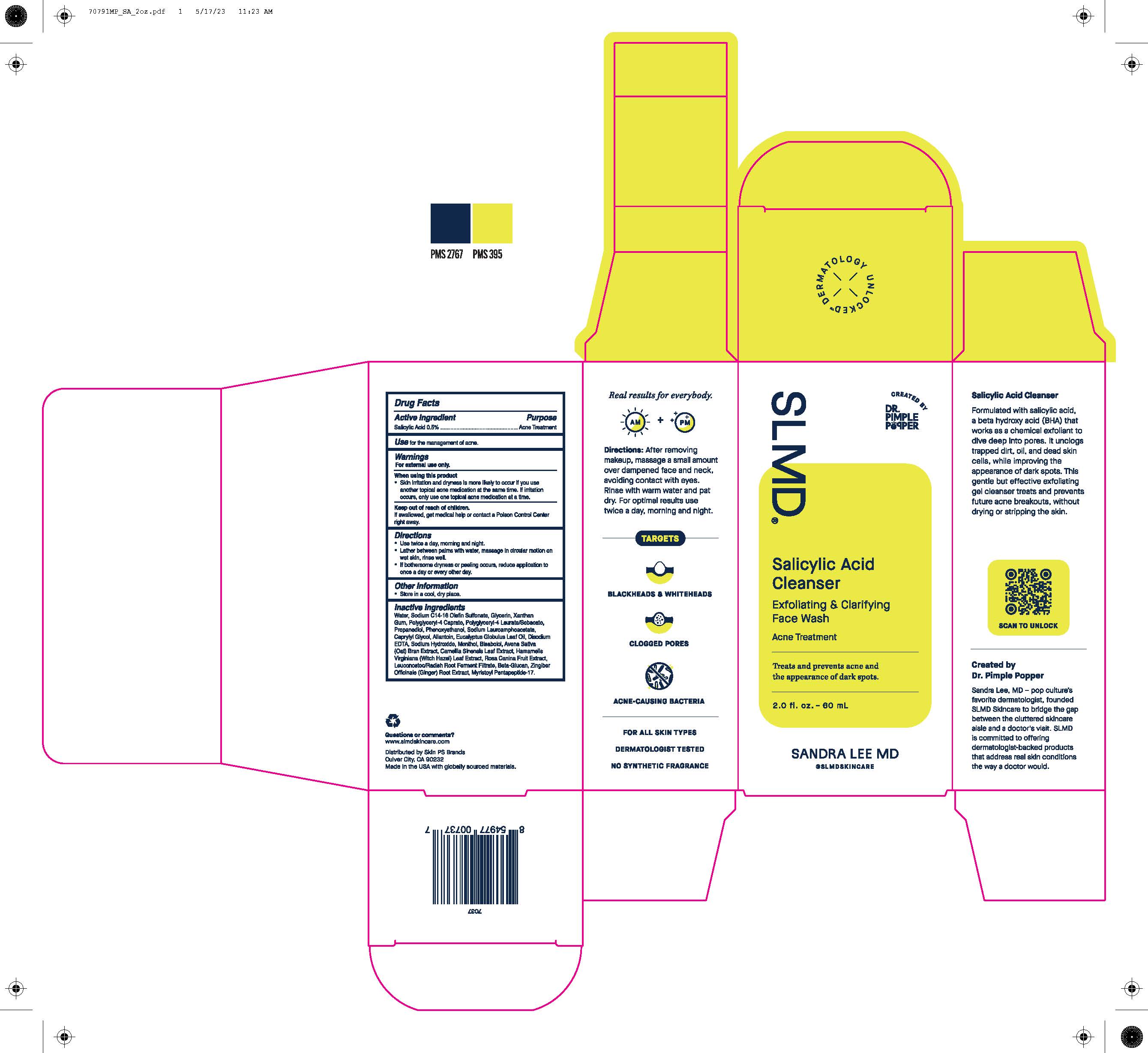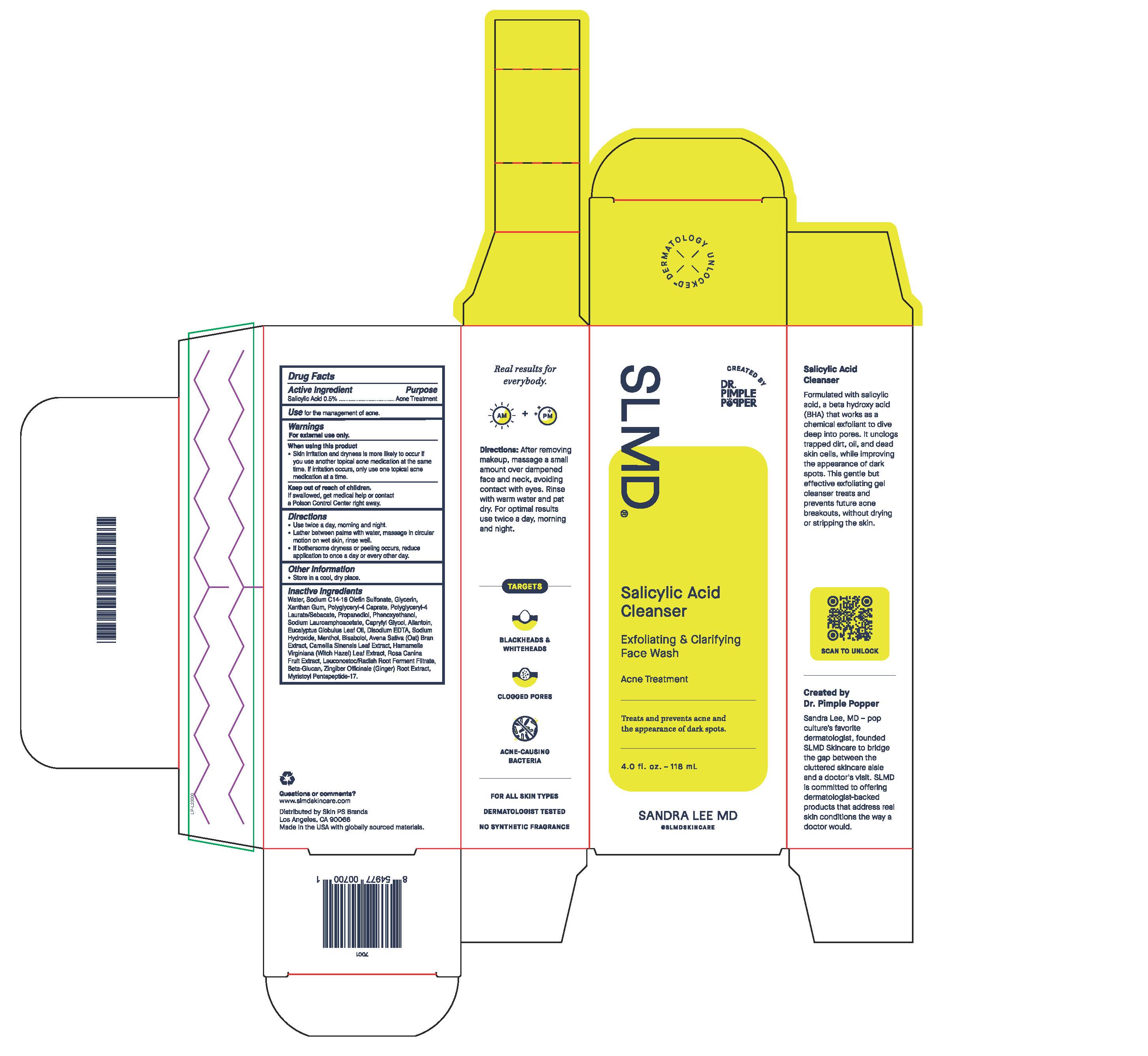 DRUG LABEL: Salicylic Acid Cleanser
NDC: 73318-7001 | Form: GEL
Manufacturer: Skin PS Brands
Category: otc | Type: HUMAN OTC DRUG LABEL
Date: 20251230

ACTIVE INGREDIENTS: SALICYLIC ACID 5 mg/1 g
INACTIVE INGREDIENTS: GLYCERIN; XANTHAN GUM; SODIUM LAUROAMPHOACETATE; EDETATE DISODIUM; SODIUM HYDROXIDE; AVENA SATIVA WHOLE; HAMAMELIS VIRGINIANA LEAF; ZINGIBER OFFICINALE WHOLE; MENTHOL; CAMELLIA SINENSIS WHOLE; POLYGLYCERYL-4 CAPRATE; ALLANTOIN; WATER; POLYGLYCERYL-4 LAURATE; PHENOXYETHANOL; SODIUM CARBOXYMETHYL .BETA.-GLUCAN (DS 0.65-0.85); LEUCONOSTOC/RADISH ROOT FERMENT FILTRATE; PROPANEDIOL; EUCALYPTUS GLOBULUS LEAF; ROSA CANINA FRUIT; SODIUM C14-16 OLEFIN SULFONATE; CAPRYLYL GLYCOL; BISABOLOL OXIDE A

Salicylic Acid Cleanser

Active Ingredient

Salicylic Acid 0.5%

Purpose

Acne Treatment

Use

Use for the management of acne.

Warnings

For external use only.

When using this product

- Skin irritation and dryness is more likely to occur if you use another topical acne medication at the same time. If irritation occurs, only use one topical acne medication at a time.

Keep out of reach of children.

If swallowed, get medical help or contact a Poison Control Center right away.

Directions

- Use twice a day, morning and night.
- Lather between palms with water, massage in circular motion on wet skin, rinse well.
- If bothersome dryness or peeling occurs, reduce application to once a day or every other day.

Other Information

- Store in a cool, dry place.

Inactive Ingredients

Water, Sodium C14-16 Olefin Sulfonate, Glycerin, Xanthan Gum, Polyglyceryl-4 Caprate, Polyglyceryl-4 Laurate/Sebacate, Propanediol, Phenoxyethanol, Sodium Lauroamphoacetate, Caprylyl Glycol, Allantoin, Eucalyptus Globulus Leaf Oil, Disodium EDTA, Sodium Hydroxide, Menthol, Bisabolol, Avena Sative (Oat) Bran Extract, Camellia Sinensis Leaf Extract, Hamamelis Virginiana (Witch Hazel) Leaf Extract, Rosa Canina Fruit Extract, Leuconostoc/Radish Root Ferment Filtrate, Beta-Glucan, Zingiber Officinale (Ginger) Root Extract, Myristoyl Pentapeptide-17.

Questions or comments?

www.slmdskincare.com

Distributed by Skin PS Brands

Los Angeles, CA 90066

Made in the USA with globally sourced materials.

Real results for everbody.

Directions: After removing makeup, massage a small amount over dampened face and neck avoiding contact with eyes. Rinse with warm water and pat dry. For optimal results use twice a day, morning and night.

TARGETS

BLACKHEADS & WHITEHEADS

CLOGGED PORES

ACNE-CAUSING BACTERIA

FOR ALL SKIN TYPES

DERMATOLOGIST TESTED

NON SYNTHETIC FRAGRANCE

Salicylic Acid Cleanser

Formulated with salicylic acid, a beta hydroxy acid (BHA) that works as a chemical exfoliant to dive deep into pores. It unclogs trapped dirt, oil, and dead skin cells, while improving the appearance of dark spots. This gentle but effective exfoliating gel cleanser treats and prevents future acne breakouts, without drying or stripping the skin.

Created by Dr. Pimple Popper

Sandra Lee, MD - pop culture's favorited dermatologist, founded SLMD Skincare to bridge the gap between the cluttered skincare aisle and a doctor's visit. SLMD is committed to offering dermatologist-backed products that address real skin conditions the way a doctor would.

SLMD

CREATED BY DR. PIMPLER POPPER

Salicylic Acid Cleaners

Exfoliating & Clarifying Face Wash

Acne Treatment

Treat and prevents acne and the appearance of dark spots.

2.0 fl. oz. - 60 mL

4.0 fl. oz. - 118 mL

SANDRA LEE MD

@SLMDSKINCARE